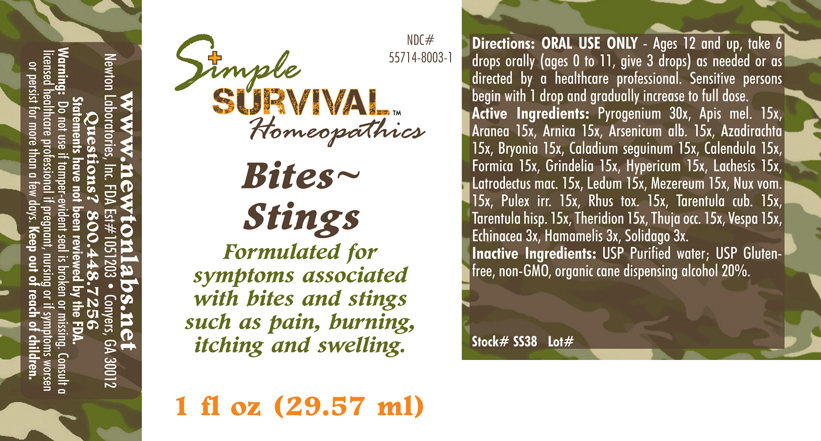 DRUG LABEL: Bites - Stings 
NDC: 55714-8003 | Form: LIQUID
Manufacturer: Newton Laboratories, Inc.
Category: homeopathic | Type: HUMAN OTC DRUG LABEL
Date: 20140415

ACTIVE INGREDIENTS: Rancid Beef 30 [hp_X]/1 mL; Apis Mellifera 15 [hp_X]/1 mL; Araneus Diadematus 15 [hp_X]/1 mL; Arnica Montana 15 [hp_X]/1 mL; Arsenic Trioxide 15 [hp_X]/1 mL; Azadirachta Indica Bark 15 [hp_X]/1 mL; Bryonia Alba Root 15 [hp_X]/1 mL; Dieffenbachia Seguine 15 [hp_X]/1 mL; Calendula Officinalis Flowering Top 15 [hp_X]/1 mL; Formica Rufa 15 [hp_X]/1 mL; Grindelia Hirsutula Flowering Top 15 [hp_X]/1 mL; Hypericum Perforatum 15 [hp_X]/1 mL; Lachesis Muta Venom 15 [hp_X]/1 mL; Latrodectus Mactans 15 [hp_X]/1 mL; Ledum Palustre Twig 15 [hp_X]/1 mL; Daphne Mezereum Bark 15 [hp_X]/1 mL; Strychnos Nux-vomica Seed 15 [hp_X]/1 mL; Pulex Irritans 15 [hp_X]/1 mL; Toxicodendron Pubescens Leaf 15 [hp_X]/1 mL; Citharacanthus Spinicrus 15 [hp_X]/1 mL; Lycosa Tarantula 15 [hp_X]/1 mL; Theridion Curassavicum 15 [hp_X]/1 mL; Thuja Occidentalis Leafy Twig 15 [hp_X]/1 mL; Vespa Crabro 15 [hp_X]/1 mL; Echinacea, Unspecified 3 [hp_X]/1 mL; Hamamelis Virginiana Root Bark/stem Bark 3 [hp_X]/1 mL; Solidago Virgaurea Flowering Top 3 [hp_X]/1 mL
INACTIVE INGREDIENTS: Alcohol

Bites - Stings

INDICATIONS & USAGE SECTION

Bites - Stings Formulated for symptoms associated with bites and stings such as pain, burning, itching and swelling.

DOSAGE & ADMINISTRATION SECTION

Directions: ORAL USE ONLY - Ages 12 and up, take 6 drops orally (ages 0 to 11, give 3 drops) as needed or as directed by a healthcare professional. Sensitive persons begin with 1 drop and gradually increase to full dose.

OTC - ACTIVE INGREDIENT SECTION

Pyrogenium 30x, Apis mel. 15x, Aranea 15x, Arnica 15x, Arsenicum alb. 15x, Azadirachta 15x, Bryonia 15x, Caladium seguinum 15x, Calendula 15, Formica 15x, Grindelia 15x, Hypericum 15x, Lachesis 15x, Latrodectus mac. 15x, Ledum 15x, Mezereum 15x, Nux vom. 15x, Pulex irr. 15x, Rhus tox. 15x, Tarentula cub. 15x, Tarentula hisp. 15x, Theridion 15x, Thuja occ. 15x, Vespa 15x, Echinacea 3x, Hamamelis 3x, Solidago 3x.

OTC - PURPOSE SECTION

Formulated for symptoms associated with bites and stings such as pain, burning, itching and swelling.

INACTIVE INGREDIENT SECTION

Inactive Ingredients: USP Purified Water; USP Gluten-free, non-GMO, organic cane dispensing alcohol 20%.

QUESTIONS SECTION

www.newtonlabs.net Newton Laboratories, Inc. FDA Est # 1051203 - Conyers, GA 30012
Questions? 1.800.448.7256

WARNINGS SECTION

Warning: Do not use if tamper - evident seal is broken or missing. Consult a licensed healthcare professional if pregnant, nursing or if symptoms worsen or persist for more than a few days. Keep out of reach of children.

OTC - PREGNANCY OR BREAST FEEDING SECTION

Consult a licensed healthcare professional if pregnant, nursing or if symptoms worsen or persist for more than a few days.

OTC - KEEP OUT OF REACH OF CHILDREN SECTION

Keep out of reach of children.